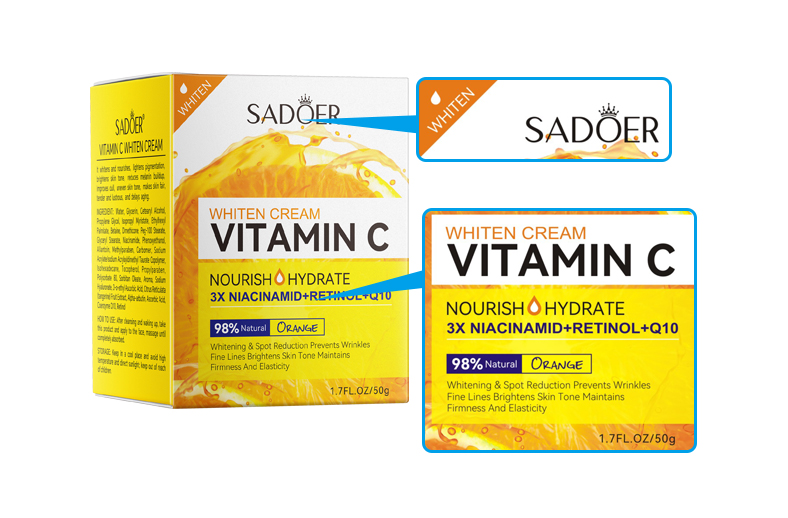 DRUG LABEL: sadoer whiten cream vit amin c
NDC: 84372-049 | Form: LOTION
Manufacturer: Shenzhen Zhumeng Times Technology Co., Ltd.
Category: otc | Type: HUMAN OTC DRUG LABEL
Date: 20240909

ACTIVE INGREDIENTS: NIACINAMIDE 5 g/50 g
INACTIVE INGREDIENTS: TANGERINE; UBIDECARENONE; METHYLPARABEN; SODIUM ACRYLATE; TAURINE; GLYCERYL STEARATE/PEG-100 STEARATE; CARBOXYMETHYLCELLULOSE; 2-ACRYLAMIDO-2-METHYL-1-PROPANESULFONIC ACID; TOCOPHEROL; SORBITAN MONOOLEATE; ISOHEXADECANE; STEARIC ACID; ASCORBIC ACID; RETINOL; ALPHA-ARBUTIN; PROPYLENE GLYCOL; GLYCERIN; PROPYLPARABEN; POLYSORBATE 80; ETHYLHEXYL PALMITATE; BETAZINE; ALLANTOIN; HYALURONATE SODIUM; WATER; ISOPROPYL MYRISTATE; DIMETHICONE; POLYETHYLENE GLYCOL 4500; PHENOXYETHANOL; CETOSTEARYL ALCOHOL; SURFOMER; 3-O-ETHYL ASCORBIC ACID

Active ingredients

Niacinamide 5%

Purpose

Whitening & Spot Reduction Prevents Wrinkles
Fine Lines Brightens Skin Tone Maintains
Firmness And Elasticity

Warnings

Before use,it is recommended that you do a
skin trial,if there is discomfort or abnormal skin
reaction,please stop using;if inadvertently into the
eyes,please immediately rinse with plenty of water.

Dosage and administration

For external use only

Do not use

Before use,it is recommended that you do a
skin trial,if there is discomfort or abnormal skin
reaction,please stop using;if inadvertently into the
eyes,please immediately rinse with plenty of water.

When using section

After cleansing and waking up,take
this product and apply to the face,massage unti
completely absorbed.

stop use

Broken or inflamed body

Keep out of reach of children.

If sxralowed, get medical help or contact a Poison Conirol Cenler ngiht away.

Inactive ingredients

Water,Glycerin,Cetearyl Alcohol

Propylene Glycol,Isopropyl Myristate,'Ethylhexy

Palritate,Betaine,Direthicone,Peg-100 stearate

Glyceryl Stearate,Phenoxyethanol

Aliantoin,Methylparaben,Carbomer, Sodium

Acrylate/sodium Acryloyldimethyl Taurate Copolymer,

Isohexadecane,Tocopherol,Propylparaben,

Polysorbate 80,Sorbitan Oleate,Aroma,Sodium

Hyaluronate,3-o-ethyl Ascorbic Acid,Citrus Reticulata

(tangerine)Fruit Extract,Alpha-arbutin,Ascorbic Acid,

Coenzyme Q10,Retinol

Uses

After cleansing and waking up,take
this product and apply to the face,massage unti
completely absorbed.